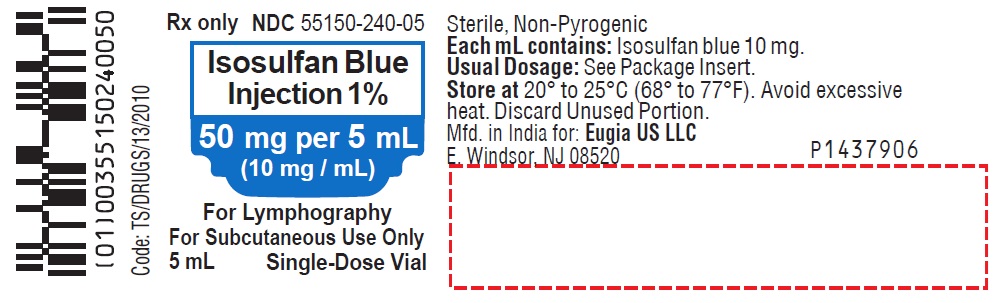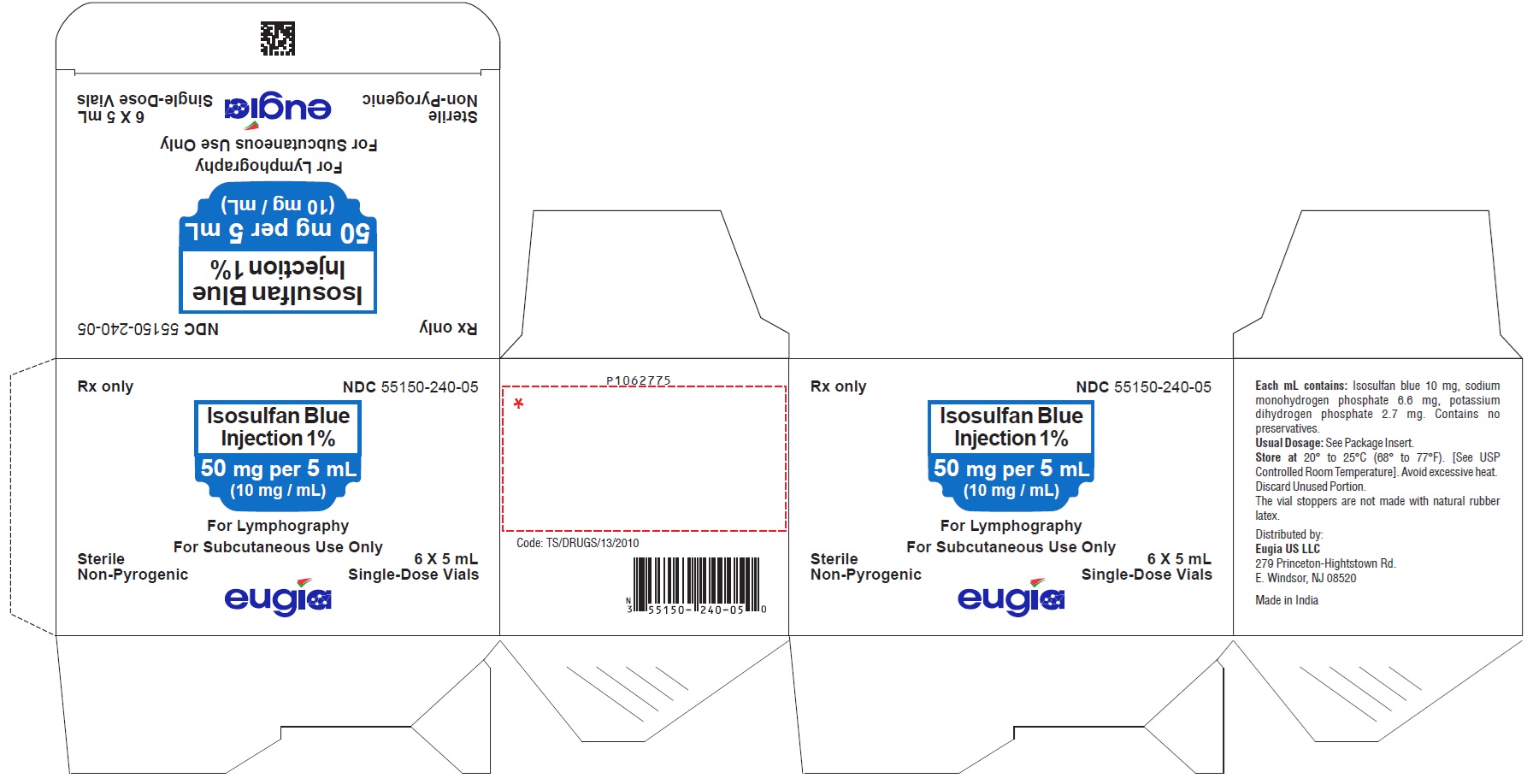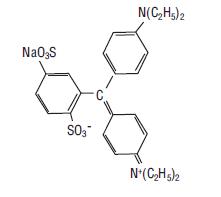 DRUG LABEL: Isosulfan Blue
NDC: 55150-240 | Form: INJECTION, SOLUTION
Manufacturer: Eugia US LLC
Category: prescription | Type: Human Prescription Drug Label
Date: 20260220

ACTIVE INGREDIENTS: ISOSULFAN BLUE 50 mg/5 mL
INACTIVE INGREDIENTS: SODIUM PHOSPHATE, DIBASIC, DIHYDRATE; POTASSIUM PHOSPHATE, MONOBASIC; WATER

HIGHLIGHTS OF PRESCRIBING INFORMATION

These highlights do not include all the information needed to use ISOSULFAN BLUE INJECTION safely and effectively. See full prescribing information for ISOSULFAN BLUE INJECTION.
ISOSULFAN BLUE injection, for subcutaneous use only
Initial U.S. Approval: 1981

1 INDICATIONS AND USAGE

Isosulfan blue injection 1% upon subcutaneous administration, delineates the lymphatic vessels draining the region of injection. It is an adjunct to lymphography in: primary and secondary lymphedema of the extremities; chyluria, chylous ascites or chylothorax; lymph node involvement by primary or secondary neoplasm; lymph node response to therapeutic modalities (1.1).

2 DOSAGE AND ADMINISTRATION

Isosulfan blue injection 1% is to be administered subcutaneously, one-half (1/2) mL into three (3) interdigital spaces of each extremity per study. A maximum dose of 3 mL (30 mg) isosulfan blue is, therefore, injected (2.1).

3 DOSAGE FORMS AND STRENGTHS

1% aqueous solution (isosulfan blue)

4 CONTRAINDICATIONS

Hypersensitivity to triphenylmethane or related compounds (4).

5 WARNINGS AND PRECAUTIONS

- Life-threatening anaphylactic reactions have occurred after isosulfan blue 1% administration. Monitor patients closely for at least 60 minutes after administration of isosulfan blue 1% (5.1).
- The admixture of isosulfan blue 1% with local anesthetics results in an immediate precipitation of 4 to 9% drug complex. Use a separate syringe for anesthetics (5.2).
- Isosulfan blue 1% interferes with measurements in peripheral blood pulse oximetry. Arterial blood gas analysis may be needed (5.3).

6 ADVERSE REACTIONS

Hypersensitivity Reactions: Hypersensitivity reactions occurring approximately 2% of patients and include life-threatening anaphylactic reactions with respiratory distress, shock, angioedema, urticaria, pruritus. A death has been reported following I.V. administration of a similar compound (6).
To report SUSPECTED ADVERSE REACTIONS, contact Eugia US LLC at 1-866-850-2876 or FDA at 1-800-FDA-1088 or www.fda.gov/medwatch.

7 DRUG INTERACTIONS

No drug interactions have been identified for isosulfan blue 1% (7).

8 USE IN SPECIFIC POPULATIONS

- Caution should be exercised when isosulfan blue 1% is administered to nursing mothers (8.3).
- Safety and effectiveness of isosulfan blue 1% in children has not been established (8.4).

FULL PRESCRIBING INFORMATION

1 INDICATIONS AND USAGE

1.1 Lymphatic Vessel Delineation

Isosulfan blue injection 1% upon subcutaneous administration, delineates lymphatic vessels draining the region of injection. It is an adjunct to lymphography in: primary and secondary lymphedema of the extremities; chyluria, chylous ascites or chylothorax; lymph node involvement by primary or secondary neoplasm; and lymph node response to therapeutic modalities.

2 DOSAGE AND ADMINISTRATION

2.1 Subcutaneous administration

Isosulfan blue injection 1% is to be administered subcutaneously, one-half (1/2) mL into three (3) interdigital spaces of each extremity per study. A maximum dose of 3 mL (30 mg) isosulfan blue is, therefore, injected.

3 DOSAGE FORMS AND STRENGTHS

1% aqueous solution (isosulfan blue)

4 CONTRAINDICATIONS

Isosulfan blue injection 1% is contraindicated in those individuals with known hypersensitivity to triphenylmethane or related compounds.

5 WARNINGS AND PRECAUTIONS

5.1 Hypersensitivity Reactions

Life-threatening anaphylactic reactions (respiratory distress, shock, angioedema) have occurred after isosulfan blue 1% administration. Reactions are more likely to occur in patients with a history of bronchial asthma, allergies, drug reactions or previous reactions to triphenylmethane dyes. Monitor patients closely for at least 60 minutes after administration of isosulfan blue 1%. Trained personnel should be available to administer emergency care including resuscitation.

5.2 Precipitation of Isosulfan Blue 1% by Lidocaine

The admixture of isosulfan blue 1% (with local anesthetics (i.e. lidocaine)) in the same syringe results in an immediate precipitation of 4 to 9% drug complex. Use a separate syringe to administer a local anesthetic.

5.3 Interference with Oxygen Saturation and Methemoglobin Measurements

Isosulfan blue 1% interferes with measurements of oxygen saturation in peripheral blood by pulse oximetry and can cause falsely low readings. The interference effect is maximal at 30 minutes and minimal generally by four hours after administration. Arterial blood gas analysis may be needed to verify decreased arterial partial pressure of oxygen.
Isosulfan blue 1% may also cause falsely elevated readings of methemoglobin by arterial blood gas analyzer. Therefore, co-oximetry may be needed to verify methemoglobin level.

6 ADVERSE REACTIONS

6.1 Postmarketing Experience

Hypersensitivity Reactions: Case series report an overall incidence of hypersensitivity reactions in approximately 2% of patients. Life-threatening anaphylactic reactions have occurred. Manifestations include respiratory distress, shock, angioedema, urticaria, pruritus. A death has been reported following administration of a similar compound employed to estimate the depth of a severe burn. Reactions are more likely to occur in patients with a personal or family history of bronchial asthma, significant allergies, drug reactions or previous reactions to triphenylmethane dyes [see Warnings and Precautions (5)].
Laboratory Tests: Isosulfan blue 1% interferes with measurements of oxygen saturation by pulse oximetry and of methemoglobin by gas analyzer [see Warnings and Precautions (5)].
Skin: transient or long-term (tattooing) blue coloration.

7 DRUG INTERACTIONS

No drug interactions have been identified with isosulfan blue 1%.

8 USE IN SPECIFIC POPULATIONS

8.3 Nursing Mothers

It is not known whether this drug is excreted in human milk. Because many drugs are excreted in human milk, caution should be exercised when isosulfan blue 1% is administered to a nursing mother.

8.4 Pediatric Use

Safety and effectiveness of isosulfan blue 1% in children have not been established.

10 OVERDOSAGE

Do not exceed indicated recommended dosage as overdosage levels have not been identified for isosulfan blue 1%.

11 DESCRIPTION

The chemical name of isosulfan blue is N-[4-[[4-(diethylamino)phenyl] (2,5-disulfophenyl) methylene]-2,5-cyclohexadien-1-ylidene]-N-ethylethanaminium hydroxide, inner salt, sodium salt. Isosulfan blue is a greenish blue color hygroscopic powder. Its structural formula is:
Isosulfan blue injection 1% is a sterile, non-pyrogenic, aqueous dark blue color solution for subcutaneous administration. Phosphate buffer in water for injection is added in sufficient quantity to yield a final pH of 6.8 to 7.4. Each mL of solution contains 10 mg isosulfan blue, 6.6 mg sodium monohydrogen phosphate and 2.7 mg potassium dihydrogen phosphate. The solution contains no preservative. Isosulfan blue injection 1% is a contrast agent for the delineation of lymphatic vessels.

12 CLINICAL PHARMACOLOGY

12.2 Pharmacodynamics

Following subcutaneous administration, isosulfan blue 1% binds to serum proteins and is picked up by the lymphatic vessels. Thus, the lymphatic vessels are delineated by the blue dye.

12.3 Pharmacokinetics

Up to 10% of the subcutaneously administered dose of isosulfan blue 1% is excreted unchanged in the urine in 24 hours in human.

13 NONCLINICAL TOXICOLOGY

13.1 Carcinogenesis, Mutagenesis, Impairment of Fertility

Long-term studies in animals have not been performed to evaluate the carcinogenic potential of isosulfan blue 1%. Reproduction studies in animals have not been conducted and, therefore, it is unknown if a problem concerning mutagenesis or impairment of fertility in either males or females exists.

13.2 Teratogenic Effects

Pregnancy Category C. Animal reproduction studies have not been conducted with isosulfan blue 1%. It is not known whether isosulfan blue 1% can cause fetal harm when administered to a pregnant woman or can affect reproduction capacity. Isosulfan blue 1% should be given to a pregnant woman only if clearly needed.

16 HOW SUPPLIED/STORAGE AND HANDLING

Isosulfan blue injection 1% is a sterile, non-pyrogenic, aqueous dark blue color solution and is supplied as follows:
Isosulfan blue injection 1%
50 mg per 5 mL (10 mg / mL):
5 mL Single-Dose Vials
in a Carton of 6 NDC 55150-240-05
Store at 20° to 25°C (68° to 77°F) [see USP Controlled Room Temperature]. Avoid excessive heat.
Discard unused portion.
The vial stoppers are not made with natural rubber latex.

17 PATIENT COUNSELING INFORMATION

Inform patients that urine color may be blue for 24 hours following administration of isosulfan blue injection 1%.
Distributed by:
Eugia US LLC
279 Princeton-Hightstown Rd.
E. Windsor, NJ 08520
Manufactured by:
Eugia Pharma Specialities Limited
Hyderabad - 500032
India

PACKAGE LABEL-PRINCIPAL DISPLAY PANEL - 1% [50 mg per 5 mL (10 mg / mL)] - Container Label

Rx only NDC 55150-240-05
Isosulfan Blue
Injection 1%
50 mg per 5 mL
(10 mg / mL)
For Lymphography
For Subcutaneous Use Only
5 mL Single-Dose Vial

PACKAGE LABEL-PRINCIPAL DISPLAY PANEL - 1% [50 mg per 5 mL (10 mg / mL)] - Container-Carton (6 Vials)

Rx only NDC 55150-240-05
Isosulfan Blue
Injection 1%
50 mg per 5 mL
(10 mg / mL)
For Lymphography
For Subcutaneous Use Only
Sterile 6 X 5 mL
Non-Pyrogenic Single-Dose Vials
eugia